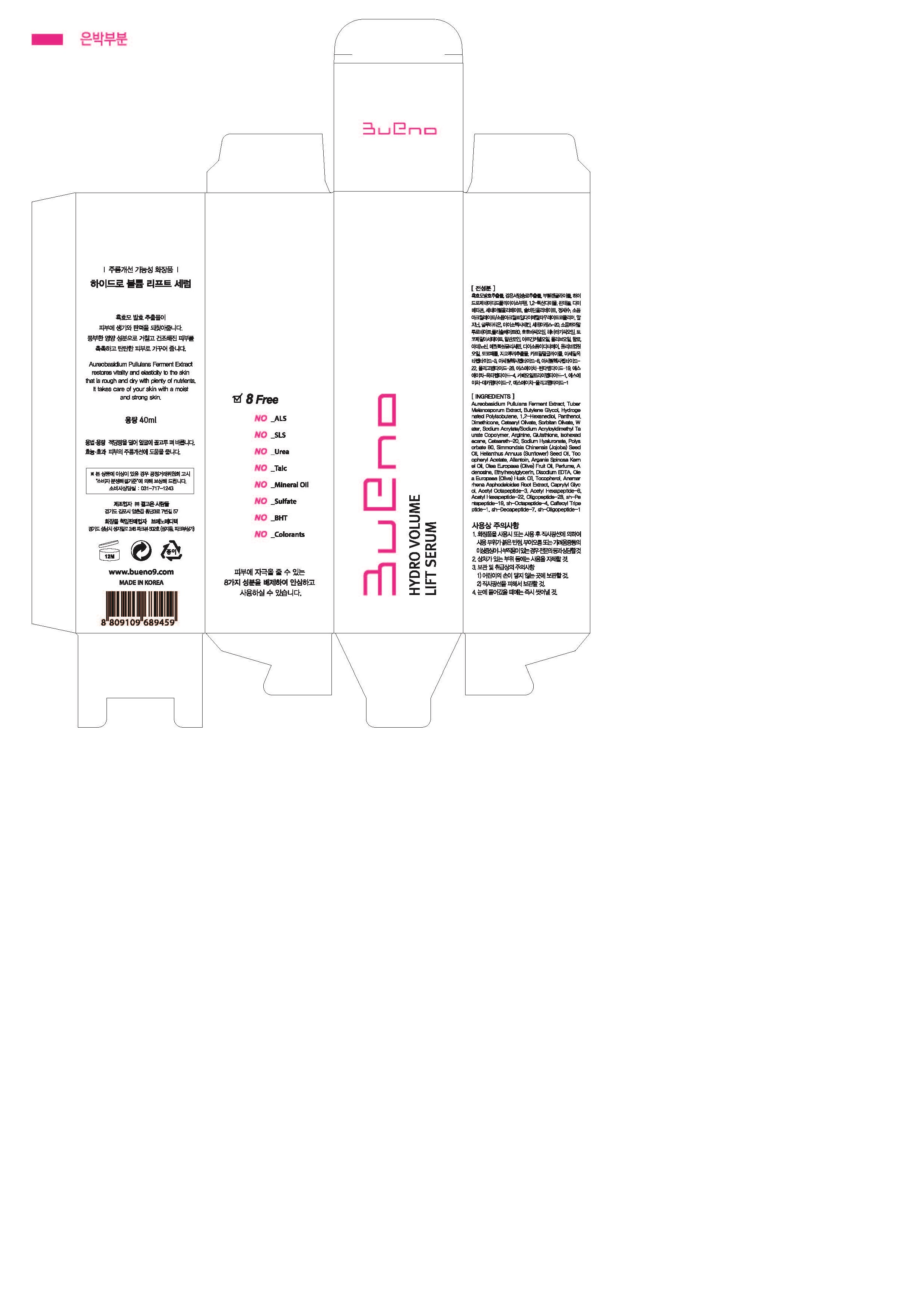 DRUG LABEL: BUENO HYDRO VOLUME LIFT SERUM
NDC: 73261-0003 | Form: LIQUID
Manufacturer: Bueno MEDITECH
Category: otc | Type: HUMAN OTC DRUG LABEL
Date: 20190803

ACTIVE INGREDIENTS: DIMETHICONE 2.5 g/100 mL
INACTIVE INGREDIENTS: BUTYLENE GLYCOL

Drug Facts

ACTIVE INGREDIENT

dimethicone

INACTIVE INGREDIENT

Aureobasidium Pullulans Ferment Extract,Tuber Melanosporum Extract,Butylene Glycol,Hydrogenated polyisobutene,

1,2-Hexanediol,Panthenol,Dimethicone,Cetearyl Olivate,Sorbitan Olivate,Water,Sodium Acrylate/Sodium Acryloyldimethyl Taurate Copolymer,Arginine,Glutathione,Isohexadecane,Ceteareth-20,Sodium Hyaluronate,Polysorbate 80,Simmondsia Chinensis (Jojoba) Seed Oil,Helianthus Annuus (Sunflower) Seed Oil,Tocopheryl Acetate,Allantoin,Argania Spinosa Kernel Oil,Olea Europaea (Olive) Fruit Oil,Perfume,Adenosine,Ethylhexylglycerin,Disodium EDTA,Olea Europaea (Olive) Husk Oil,

Tocopherol,Anemarrhena Asphodeloides Root Extract,Caprylyl Glycol,Acetyl Octapeptide-3,Acetyl Hexapeptide-8,Acetyl Hexapeptide-22,Oligopeptide-28,sh-Pentapeptide-19,sh-Octapeptide-4,Caffeoyl Tripeptide-1,sh-Decapeptide-7,Sh-Oligopeptide-1

PURPOSE

anti-wrinkle

keep out of reach of the children

INDICATIONS AND USAGE

apply proper amount to the skin

WARNINGS

discontinue use if irritation or rash appears

avoid using on injured skin

keep out of childres

store out of direct sunlight

DOSAGE AND ADMINISTRATION

for topical use only